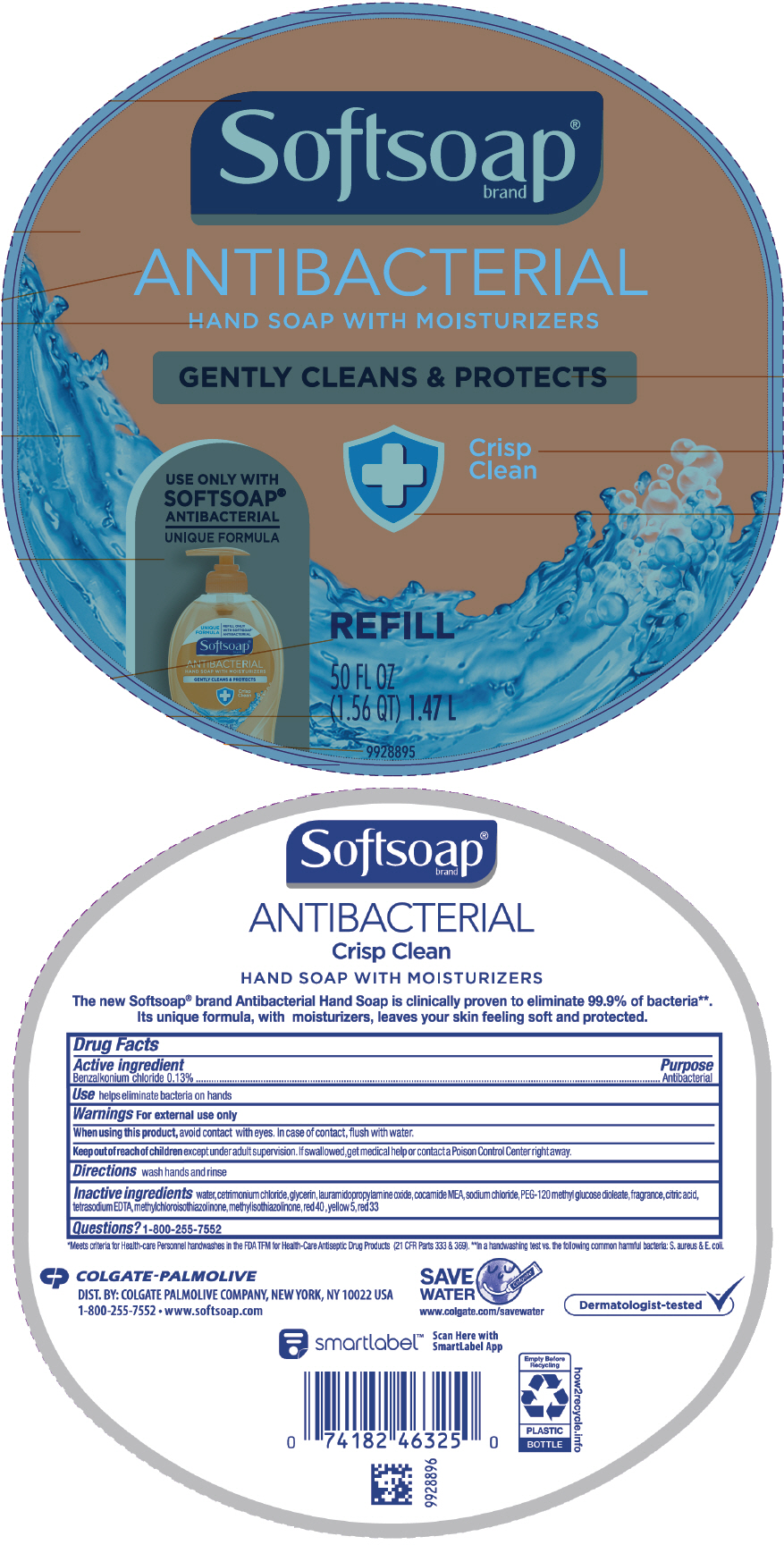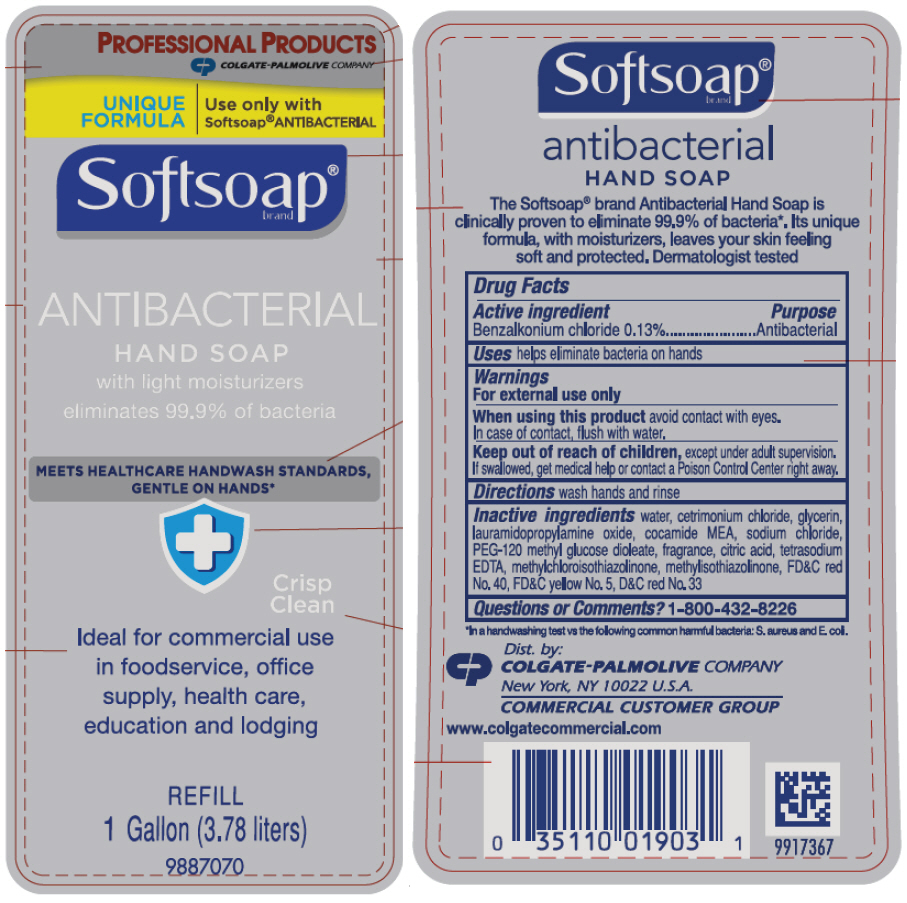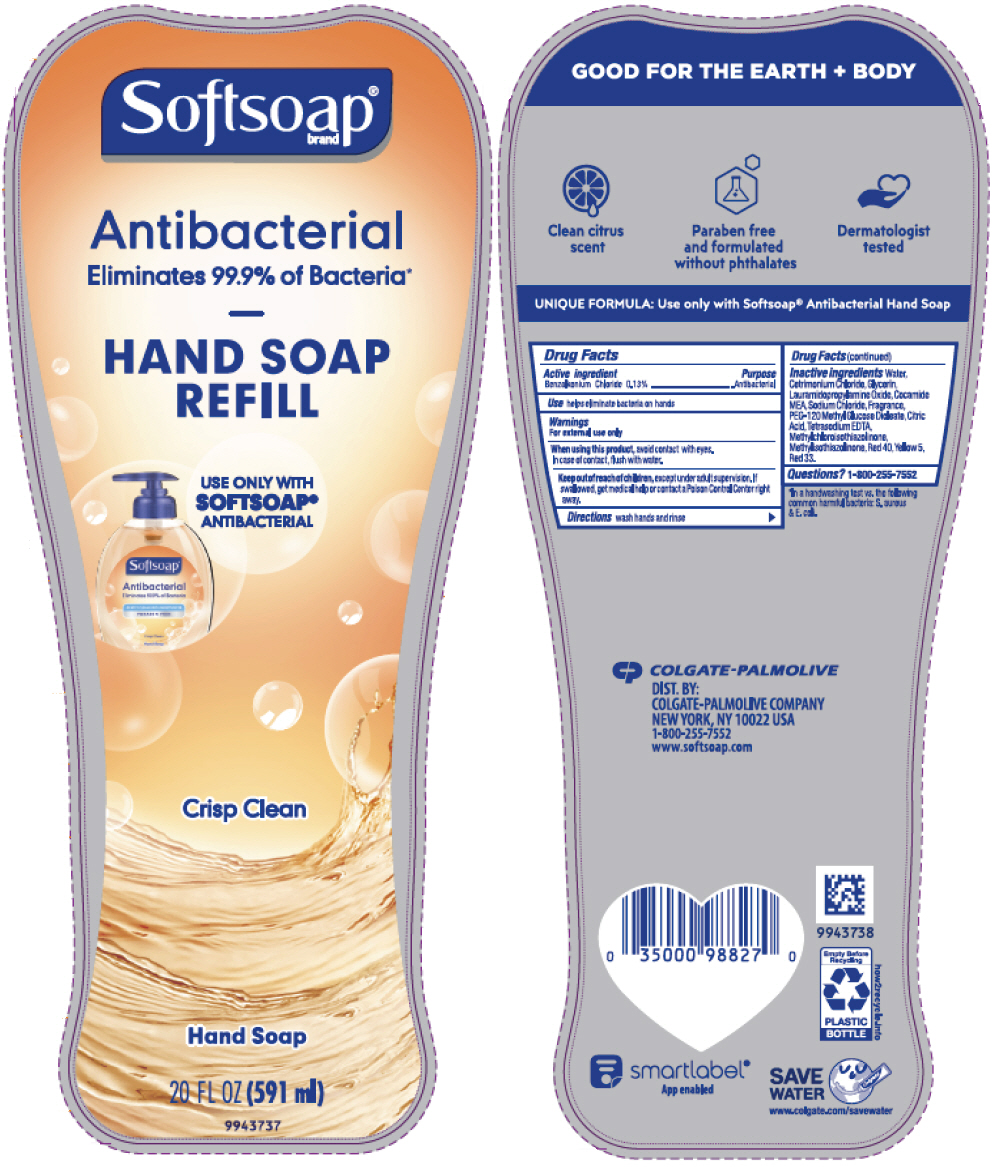 DRUG LABEL: SoftSoap Antibacterial with moisturizers Crisp Clean
NDC: 35000-086 | Form: LIQUID
Manufacturer: Colgate-Palmolive Company
Category: otc | Type: HUMAN OTC DRUG LABEL
Date: 20200901

ACTIVE INGREDIENTS: BENZALKONIUM CHLORIDE 1.33 mg/1 mL
INACTIVE INGREDIENTS: WATER; CETRIMONIUM CHLORIDE; GLYCERIN; LAURAMIDOPROPYLAMINE OXIDE; COCO MONOETHANOLAMIDE; SODIUM CHLORIDE; PEG-120 METHYL GLUCOSE DIOLEATE; CITRIC ACID MONOHYDRATE; EDETATE SODIUM; METHYLCHLOROISOTHIAZOLINONE; METHYLISOTHIAZOLINONE; FD&C RED NO. 40; FD&C YELLOW NO. 5; D&C RED NO. 33

SoftSoap® Antibacterial Hand Soap with moisturizers Crisp Clean

Drug Facts

Active ingredient

Benzalkonium chloride 0.13%

Purpose

Antibacterial

Use

helps eliminate bacteria on hands

Warnings

For external use only

When using this product, avoid contact with eyes. In case of contact, flush with water.

Keep out of reach of children except under adult supervision. If swallowed, get medical help or contact a Poison Control Center right away.

Directions

wash hands and rinse

Inactive ingredients

water, cetrimonium chloride, glycerin, lauramidopropylamine oxide, cocamide MEA, sodium chloride, PEG-120 methyl glucose dioleate, fragrance, citric acid, tetrasodium EDTA, methylchloroisothiazolinone, methylisothiazolinone, red 40, yellow 5, red 33

Questions?

1-800-255-7552

DIST. BY: COLGATE PALMOLIVE COMPANY, NEW YORK, NY 10022 USA

PRINCIPAL DISPLAY PANEL - 1.47 L Bottle Label

Softsoap®
brand

ANTIBACTERIAL
HAND SOAP WITH MOISTURIZERS

GENTLY CLEANS & PROTECTS

Crisp
Clean

USE ONLY WITH
SOFTSOAP®
ANTIBACTERIAL

UNIQUE FORMULA

REFILL

50 FL OZ
(1.56 QT) 1.47 L

9928895

PRINCIPAL DISPLAY PANEL - 3.78 liter Bottle Label

PROFESSIONAL PRODUCTS

COLGATE-PALMOLIVE COMPANY

UNIQUE
FORMULA

Use only with
Softsoap® ANTIBACTERIAL

Softsoap®
brand

ANTIBACTERIAL
HAND SOAP
with light moisturizers
eliminates 99.9% of bacteria

MEETS HEALTHCARE HANDWASH STANDARDS,
GENTLE ON HANDS*

Crisp
Clean

Ideal for commercial use
in foodservice, office
supply, health care,
education and lodging

REFILL
1 Gallon (3.78 liters)

9887070

PRINCIPAL DISPLAY PANEL - 591 ml Bottle Label

Softsoap®
brand

Antibacterial
Eliminates 99.9% of Bacteria*

HAND SOAP
REFILL

USE ONLY WITH
SOFTSOAP®
ANTIBACTERIAL

Crisp Clean

Hand Soap

20 FL OZ (591 ml)

9943737